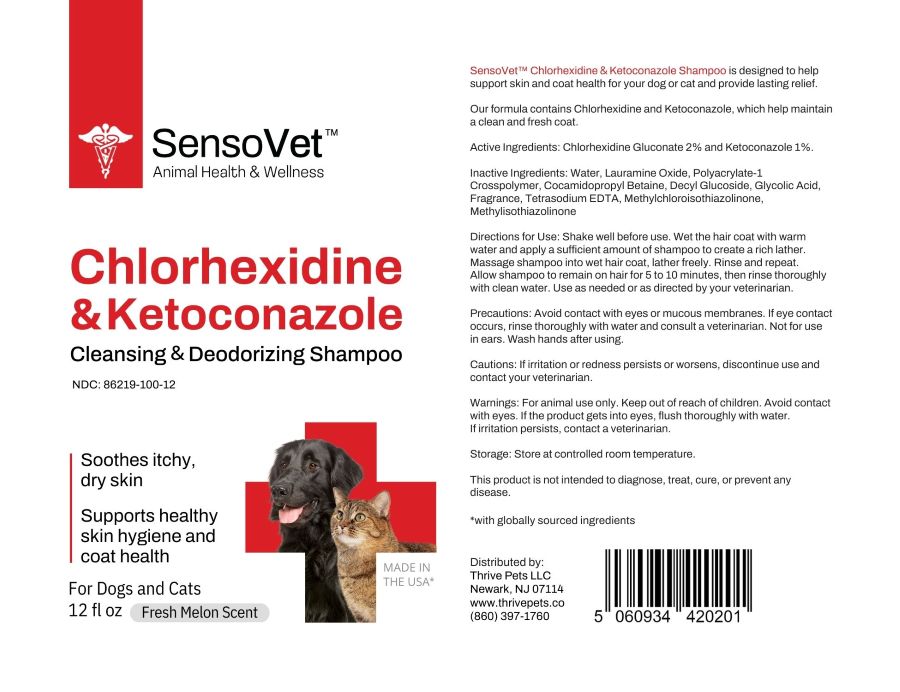 DRUG LABEL: Chlorhexidine and Ketoconazole
NDC: 86219-100 | Form: Shampoo
Manufacturer: Thrive Pets LLC
Category: animal | Type: OTC ANIMAL DRUG LABEL
Date: 20250320

ACTIVE INGREDIENTS: CHLORHEXIDINE GLUCONATE 2 g/100 mL; Ketoconazole 1 g/100 mL
INACTIVE INGREDIENTS: Water; Lauramine Oxide; Polyacrylate-1 Crosspolymer; Cocamidopropyl Betaine; Decyl Glucoside; Glycolic Acid; Tetrasodium EDTA; Methylchloroisothiazolinone; Methylisothiazolinone

SensoVet Chlorhexidine and Ketoconazole

DESCRIPTION

SensoVet™ Chlorhexidine & Ketoconazole Shampoo is designed to help support skin and coat health for your dog or cat and provide lasting relief.
Our formula contains Chlorhexidine and Ketoconazole, which help maintain a clean and fresh coat.

Active Ingredients:

Chlorhexidine Gluconate 2%
Ketoconazole 1%

Inactive Ingredients:

Water, Lauramine Oxide, Polyacrylate-1 Crosspolymer, Cocamidopropyl Betaine, Decyl Glucoside, Glycolic Acid, Fragrance, Tetrasodium EDTA, Methylchloroisothiazolinone, Methylisothiazolinone

Indications

- For dogs and cats.
- Supports healthy skin hygiene and coat health.
- Soothes itchy, dry skin.
- Cleansing & deodorizing shampoo.

Directions for Use:

- Shake well before use. Wet the hair coat with warm water and apply a sufficient amount of shampoo to create a rich lather.
- Massage shampoo into wet hair coat, lather freely. Rinse and repeat.
- Allow shampoo to remain on hair for 5 to 10 minutes, then rinse thoroughly with clean water. Use as needed or as directed by your veterinarian.

Precautions:

- Avoid contact with eyes or mucous membranes.
- If eye contact occurs, rinse thoroughly with water and consult a veterinarian.
- Not for use in ears.
- Wash hands after using.

Cautions:

- If irritation or redness persists or worsens, discontinue use and contact your veterinarian.

Warnings:

- For animal use only.
- Keep out of reach of children.
- Avoid contact with eyes.
- If the product gets into eyes, flush thoroughly with water.
- If irritation persists, contact a veterinarian.

STORAGE AND HANDLING

- Store at controlled room temperature.
- This product is not intended to diagnose, treat, cure, or prevent any disease.
- with globally sourced ingredients

Distributed by:

Thrive Pets LLC
Newark, NJ 07114
www.thrivepets.co
(860) 397-1760

PRINCIPAL DISPLAY PANEL - 12 fl oz

SensoVetTM

Animal Health & Wellness

Chlorhexidine & Ketoconazole

Cleansing & Deodorizing Shampoo

Soothes itchy, dry skin

Supports healthy skin hygiene and coat health

for Dogs and Cats

12 fl oz

Fresh Melon Scent